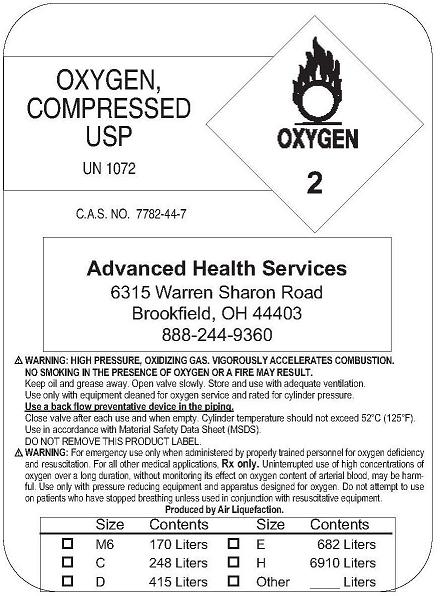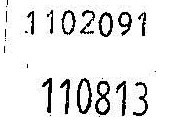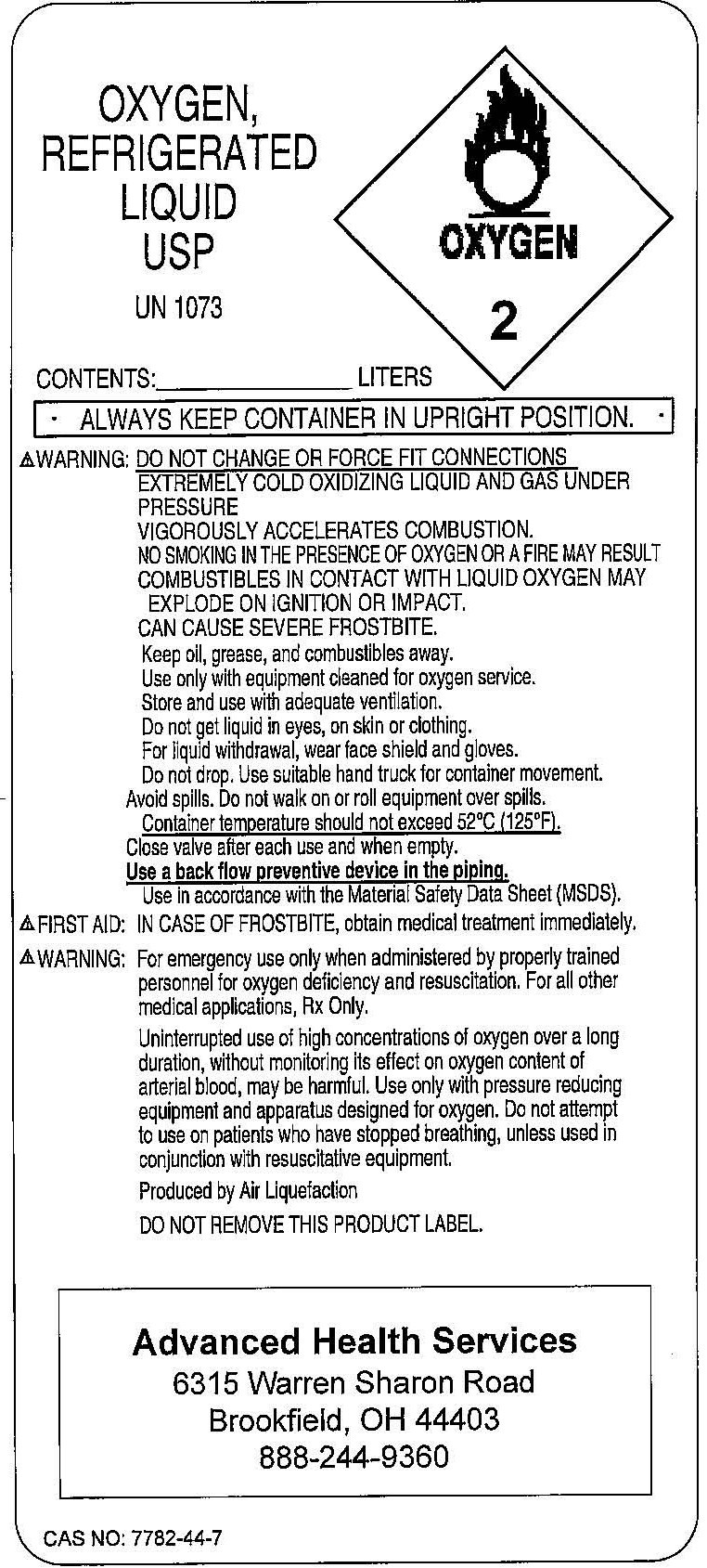 DRUG LABEL: Oxygen
NDC: 65076-0001 | Form: GAS
Manufacturer: Advanced Health Services, Inc. 
Category: prescription | Type: HUMAN PRESCRIPTION DRUG LABEL
Date: 20091109

ACTIVE INGREDIENTS: Oxygen 99 L/100 L

Oxygen